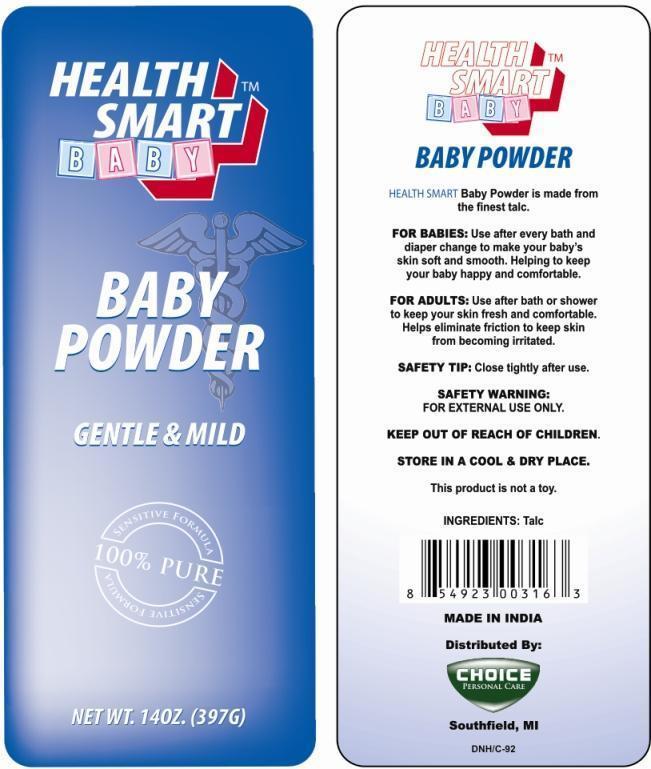 DRUG LABEL: Health Smart Baby
NDC: 52862-010 | Form: POWDER
Manufacturer: Home Smart Products
Category: otc | Type: HUMAN OTC DRUG LABEL
Date: 20200813

ACTIVE INGREDIENTS: TALC 1 g/1 g
INACTIVE INGREDIENTS: FRAGRANCE CLEAN ORC0600327 0.001 g/1 g

Active Ingredient

Talc 100%

Purpose

Skin Protectant

Uses

For Babies: Use after every bath and diaper change to make your baby’s skin soft and smooth. Helping to keep your baby happy and comfortable.

For Adults: Use after bath or shower to keep your skin fresh and comfortable. Helps eliminate friction to keep skin from becoming irritated.

WARNING

For external use only. Avoid contact with eyes discontinue if irritation developes.

Keep Out of Reach of Children

Children if swallowed get medical help or contact Poison Control Center right away.

Directions

Apply product liberally, as often as necessary

Storage

Store in a cool and dry place. Close tightly after use.

Inactive Ingredient

Fragrance

PRINCIPAL DISPLAY PANEL

Health Smart Baby Powder

NET WT. 14 OZ (397G)